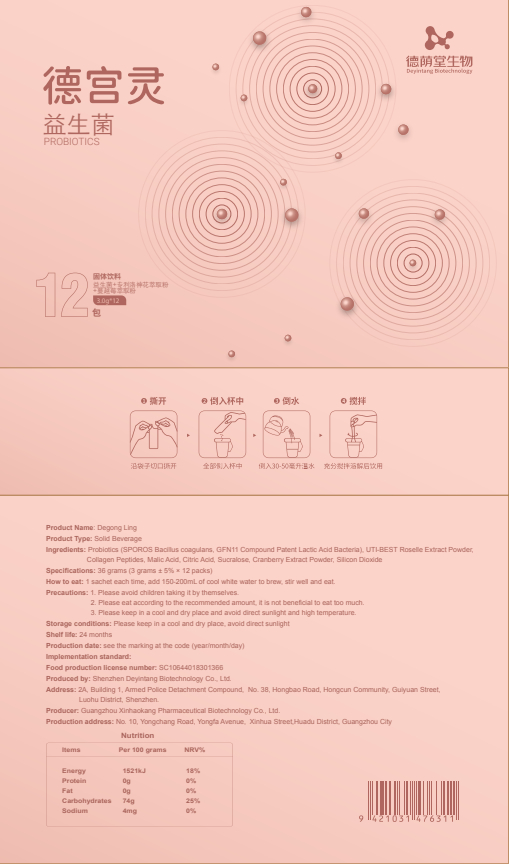 DRUG LABEL: Degong Ling
NDC: 82570-011 | Form: POWDER
Manufacturer: Shenzhen Deyintang Biotechnology Co., Ltd.
Category: otc | Type: HUMAN OTC DRUG LABEL
Date: 20220221

ACTIVE INGREDIENTS: HIBISCUS SABDARIFFA CALYX 7 g/100 g; COLLAGEN, SOLUBLE, FISH SKIN 35 g/100 g
INACTIVE INGREDIENTS: BIFIDOBACTERIUM ANIMALIS LACTIS; LACTOBACILLUS PARACASEI; LACTOBACILLUS ACIDOPHILUS; MALIC ACID; CITRIC ACID MONOHYDRATE; STREPTOCOCCUS THERMOPHILUS; LACTOBACILLUS RHAMNOSUS; BIFIDOBACTERIUM BIFIDUM; BIFIDOBACTERIUM LONGUM; CRANBERRY; SUCRALOSE; SILICON DIOXIDE; LIMOSILACTOBACILLUS REUTERI

ACTIVE INGREDIENT

Probiotics (SPOROS Baclus coagulans, GFN11 Compound Patent Lactic Acid Bacteria),UT-BEST Roselle Extract Powder,
Collagen Peptides

INACTIVE INGREDIENT

Malic Acid, Citric Acid, Sucralose, Cranberry Extract Powder, Silicon Dioxide

PURPOSE

health care

Please avoid children taking it by themselves.

How to eat

1 sachet each time, add 150-200mL of cool white water to brew, stir well and eat.

INDICATIONS AND USAGE

Please eat according to the recommended amount, it is not beneficial to eat too much

Storage conditions

Please keep in a cool and dry place, avoid direct sunlight

WARNINGS

1.Please avoid children taking it by themselves.
2.Please eat according to the recommended amount, it is not beneficial to eat too much.

3.Please keep in a cool and dry place and avoid direct sunlight and high temperature.